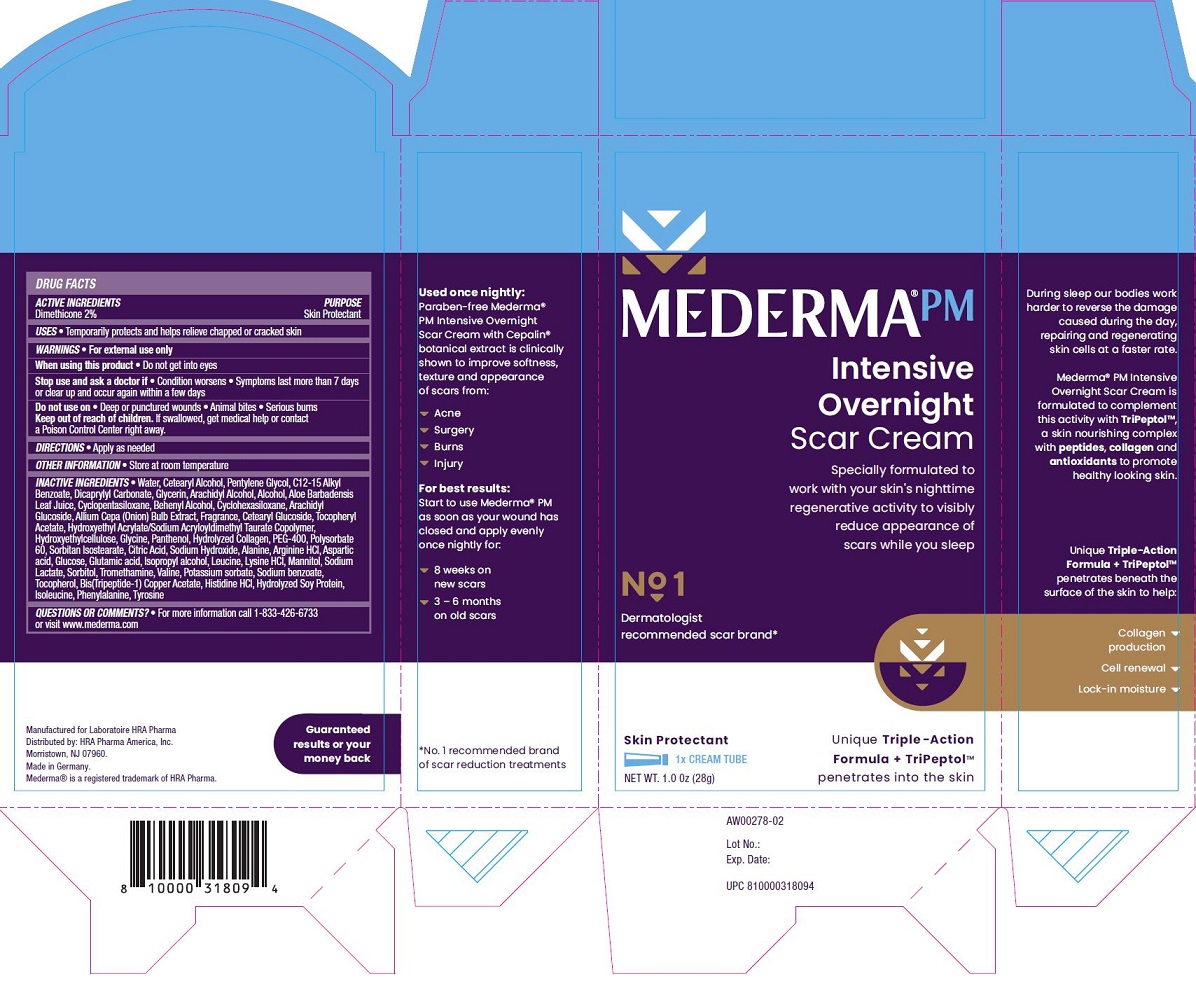 DRUG LABEL: Mederma PM
NDC: 73302-203 | Form: CREAM
Manufacturer: HRA PHARMA AMERICA, INC.
Category: otc | Type: HUMAN OTC DRUG LABEL
Date: 20250125

ACTIVE INGREDIENTS: Dimethicone 20 mg/1 g
INACTIVE INGREDIENTS: water; Cetostearyl Alcohol; Pentylene Glycol; Alkyl (C12-15) Benzoate; Dicaprylyl Carbonate; Glycerin; Arachidyl alcohol; Alcohol; Aloe Vera Leaf; Cyclomethicone 5; Docosanol; Cyclomethicone 6; Arachidyl glucoside; Onion; Cetearyl Glucoside; .Alpha.-Tocopherol Acetate; Hydroxyethyl acrylate/Sodium acryloyldimethyl Taurate Copolymer (100000 MPA.S AT 1.5%); Hydroxyethyl Cellulose (2000 MPA.S AT 1%); Glycine; Panthenol; Bovine Type I Collagen; POLYETHYLENE GLYCOL 400; Polysorbate 60; Sorbitan Isostearate; Citric Acid Monohydrate; Sodium Hydroxide; Alanine; Arginine Hydrochloride; Aspartic Acid; Anhydrous Dextrose; Glutamic Acid; Isopropyl Alcohol; Leucine; Lysine Hydrochloride; Mannitol; Sodium Lactate; Sorbitol; Tromethamine; Valine; Potassium Sorbate; Sodium Benzoate; Tocopherol; Prezatide Copper Acetate; Histidine Monohydrochloride; Soy Protein; Isoleucine; Phenylalanine; Tyrosine

MEDERMA PM DRUG FACTS

Active Ingredients

Dimethicone 2%

Purpose

Skin Protectant

Uses

- Temporarily protects and helps relieve chapped or cracked skin

Warnings

- For external use only

When using this product

- Do not get into eyes

Stop use and ask a doctor if

- Condition worsens
- Symptoms last more than 7 days or clear up and occur again within a few days

Do not use on

- Deep or punctured wounds
- Animal bites
- Serious burns

Keep out of reach of children.

If swallowed, get medical help or contact a Poison Control Center right away.

Directions

Apply as needed

Other Information

- Store at room temperature

Inactive Ingredients

- Water, Cetearyl Alcohol, Pentylene Glycol, C12-15 Alkyl Benzoate, Dicaprylyl Carbonate, Glycerin, Arachidyl Alcohol, Alcohol, Aloe Barbadensis Leaf Juice, Cyclopentasiloxane, Behenyl Alcohol, Cyclohexasiloxane, Arachidyl Glucoside, Allium Cepa (Onion) Bulb Extract, Fragrance, Cetearyl Glucoside, Tocopheryl Acetate, Hydroxyethyl Acrylate/Sodium Acryloyldimethyl Taurate Copolymer, Hydroxyethylcellulose, Glycine, Panthenol, Hydrolyzed Collagen, PEG-400, Polysorbate 60, Sorbitan Isostearate, Citric Acid, Sodium Hydroxide, Alanine, Arginine HCl, Aspartic acid, Glucose, Glutamic acid, Isopropyl alcohol, Leucine, Lysine HCl, Mannitol, Sodium Lactate, Sorbitol, Tromethamine, Valine, Potassium sorbate, Sodium benzoate, Tocopherol, Bis(Tripeptide-1) Copper Acetate, Histidine HCl, Hydrolyzed Soy Protein, Isoleucine, Phenylalanine, Tyrosine

Questions or Comments

- For more information call 1-833-426-6733 or visit www.mederma.com

PRINCIPAL DISPLAY PANEL

MEDERMA® PM
Intensive Overnight Scar Cream
Specially formulated to work with your skin's nighttime regenerative activity to visibly reduce appearance of scars while you sleep
No 1 Dermatologist recommended scar brand
Skin Protectant
1x CREAM TUBE
NET WT. 1.0 Oz (28g)
Unique Triple - Action Formula + TriPeptol™ penetrates into the skin